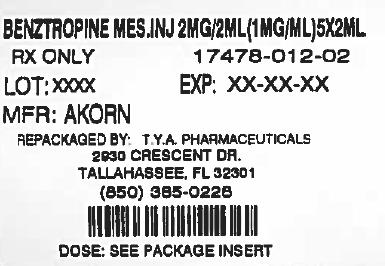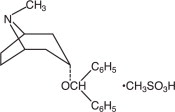 DRUG LABEL: Benztropine Mesylate
NDC: 64725-0012 | Form: INJECTION
Manufacturer: TYA Pharmaceuticals
Category: prescription | Type: HUMAN PRESCRIPTION DRUG LABEL
Date: 20130531

ACTIVE INGREDIENTS: Benztropine Mesylate 1 mg/1 mL
INACTIVE INGREDIENTS: SODIUM CHLORIDE 9 mg/1 mL; WATER

Benztropine Mesylate Injection, USP

Rx only

DESCRIPTION

Benztropine mesylate is a synthetic compound containing structural features found in atropine and diphenhydramine.

It is designated chemically as 8-azabicyclo[3.2.1] octane, 3-(diphenylmethoxy)-, , methanesulfonate. Its empirical formula is C H NO•CH O S, and its structural formula is: endo212543

Benztropine mesylate is a crystalline white powder, very soluble in water, and has a molecular weight of 403.54.

Benztropine mesylate injection, USP is supplied as a sterile injection for intravenous and intramuscular use.

Each milliliter of the injection contains:

Benztropine mesylate . . . . . . . . . . . . . . . . . . . . . . . . . . . . . . . . . . . . . . . . . . . . . . . . . . . . . 1 mg

Sodium chloride . . . . . . . . . . . . . . . . . . . . . . . . . . . . . . . . . . . . . . . . . . . . . . . . . . . . . . . . . 9 mg

Water for injection q.s. . . . . . . . . . . . . . . . . . . . . . . . . . . . . . . . . . . . . . . . . . . . . . . . . . . . . 1 mL

CLINICAL PHARMACOLOGY

Benztropine mesylate injection, USP possesses both anticholinergic and antihistaminic effects, although only the former have been established as therapeutically significant in the management of parkinsonism.

In the isolated guinea pig ileum, the anticholinergic activity of this drug is about equal to that of atropine; however, when administered orally to unanesthetized cats, it is only about half as active as atropine.

In laboratory animals, its antihistaminic activity and duration of action approach those of pyrilamine maleate.

INDICATIONS

For use as an adjunct in the therapy of all forms of parkinsonism (see). DOSAGE AND ADMINISTRATION

Useful also in the control of extrapyramidal disorders (except tardive dyskinesia – see) due to neuroleptic drugs (e.g., phenothiazines). PRECAUTIONS

CONTRAINDICATIONS

Hypersensitivity to any component of benztropine mesylate injection, USP.

Because of its atropine-like side effects, this drug is contraindicated in pediatric patients under three years of age, and should be used with caution in older pediatric patients.

WARNINGS

Safe use in pregnancy has not been established.

Benztropine mesylate injection, USP may impair mental and/or physical abilities required for performance of hazardous tasks, such as operating machinery or driving a motor vehicle.

When benztropine mesylate injection, USP is given concomitantly with phenothiazines, haloperidol, or other drugs with anticholinergic or antidopaminergic activity, patients should be advised to report gastrointestinal complaints, fever or heat intolerance promptly. Paralytic ileus, hyperthermia and heat stroke, all of which have sometimes been fatal, have occurred in patients taking anticholinergic-type antiparkinsonism drugs, including benztropine mesylate injection, in combination with phenothiazines and/or tricyclic antidepressants.

Since benztropine mesylate injection contains structural features of atropine, it may produce anhidrosis. For this reason, it should be administered with caution during hot weather, especially when given concomitantly with other atropine-like drugs to the chronically ill, the alcoholic, those who have central nervous system disease, and those who do manual labor in a hot environment. Anhidrosis may occur more readily when some disturbance of sweating already exists. If there is evidence of anhidrosis, the possibility of hyperthermia should be considered. Dosage should be decreased at the discretion of the physician so that the ability to maintain body heat equilibrium by perspiration is not impaired. Severe anhidrosis and fatal hyperthermia have occured.

PRECAUTIONS

GENERAL PRECAUTIONS

Since benztropine mesylate injection, USP has cumulative action, continued supervision is advisable. Patients with a tendency to tachycardia and patients with prostatic hypertrophy should be observed closely during treatment. General:

Dysuria may occur, but rarely becomes a problem. Urinary retention has been reported with benztropine mesylate injection, USP.

The drug may cause complaints of weakness and inability to move particular muscle groups, especially in large doses. For example, if the neck has been rigid and suddenly relaxes, it may feel weak, causing some concern. In this event, dosage adjustment is required.

Mental confusion and excitement may occur with large doses, or in susceptible patients. Visual hallucinations have been reported occasionally. Furthermore, in the treatment of extrapyramidal disorders due to neuroleptic drugs (e.g., phenothiazines), in patients with mental disorders, occasionally there may be intensification of mental symptoms. In such cases, antiparkinsonian drugs can precipitate a toxic psychosis. Patients with mental disorders should be kept under careful observation, especially at the beginning of treatment or if dosage is increased.

Tardive dyskinesia may appear in some patients on long-term therapy with phenothiazines and related agents, or may occur after therapy when these drugs have been discontinued. Antiparkinsonism agents do not alleviate the symptoms of tardive dyskinesia, and in some instances may aggravate them. Benztropine mesylate injection, USP is not recommended for use in patients with tardive dyskinesia.

The physician should be aware of the possible occurrence of glaucoma. Although the drug does not appear to have any adverse effect on simple glaucoma, it probably should not be used in angle-closure glaucoma.

DRUG INTERACTIONS

Antipsychotic drugs such as phenothiazines or haloperidol; tricyclic antidepressants (see). Drug Interactions: WARNINGS

PEDIATRIC USE

Because of the atropine-like side effects, benztropine mesylate injection, USP should be used with caution in pediatric patients over three years of age (see). Pediatric use: CONTRAINDICATIONS

GERIATRIC USE

Clinical studies of benztropine mesylate did not include sufficient numbers of subjects aged 65 and over to determine whether may respond differently from younger subjects. Other reported clinical experience has not identified differences in responses between the elderly and younger patients. In general, dose selection for an elderly patient should start at the low end of the dosing range (see) and the dose should be increased only as needed with monitoring for the emergence of adverse events (see and). Geriatric Use: DOSAGE AND ADMINISTRATIONPRECAUTIONSADVERSE REACTIONS

ADVERSE REACTIONS

The adverse reactions below, most of which are anticholinergic in nature, have been reported and within each category are listed in order of decreasing severity.

Tachycardia. Cardiovascular:

Paralytic ileus, constipation, vomiting, nausea, dry mouth. Digestive:

If dry mouth is so severe that there is difficulty in swallowing or speaking, or loss of appetite and weight, reduce dosage, or discontinue the drug temporarily.

Slight reduction in dosage may control nausea and still give sufficient relief of symptoms. Vomiting may be controlled by temporary discontinuation, followed by resumption at a lower dosage.

Toxic psychosis, including confusion, disorientation, memory impairment, visual hallucinations; exacerbation of pre-existing psychotic symptoms; nervousness; depression; listlessness; numbness of fingers. Nervous System:

Blurred vision, dilated pupils. Special Senses:

Urinary retention, dysuria. Urogenital:

Occasionally, an allergic reaction, e.g., skin rash, develops. If this cannot be controlled by dosage reduction, the medication should be discontinued. Metabolic/Immune or Skin:

Heat stroke, hyperthermia, fever. Other:

To report SUSPECTED ADVERSE REACTIONS, contact Akorn, Inc. at 1-800-932-5676 or FDA at 1-800-FDA-1088 or www.fda.gov/medwatch.

DOSAGE AND ADMINISTRATION

Since there is no significant difference in onset of effect after intravenous or intramuscular injection, usually there is no need to use the intravenous route. The drug is quickly effective after either route, with improvement sometimes noticeable a few minutes after injection. In emergency situations, when the condition of the patient is alarming, 1 to 2 mL of the injection normally will provide quick relief. If the parkinsonian effect begins to return, the dose can be repeated.

Because of cumulative action, therapy should be initiated with a low dose which is increased gradually at five or six-day intervals to the smallest amount necessary for optimal relief. Increases should be made in increments of 0.5 mg, to a maximum of 6 mg, or until optimal results are obtained without excessive adverse reactions.

The following dosing guidelines were written in reference to both benztropine mesylate tablets and COGENTIN Injection. Benztropine mesylate tablets should be used when patients are able to take oral medication. Postencephalitic and Idiopathic Parkinsonism:

The usual daily dose is 1 to 2 mg, with a range of 0.5 to 6 mg parenterally.

As with any agent used in parkinsonism, dosage must be individualized according to age and weight, and the type of parkinsonism being treated. Generally, older patients, and thin patients cannot tolerate large doses. Most patients with postencephalitic parkinsonism need fairly large doses and tolerate them well. Patients with a poor mental outlook are usually poor candidates for therapy.

In idiopathic parkinsonism, therapy may be initiated with a single daily dose of 0.5 to 1 mg at bedtime. In some patients, this will be adequate; in others 4 to 6 mg a day may be required.

In postencephalitic parkinsonism, therapy may be initiated in most patients with 2 mg a day in one or more doses. In highly sensitive patients, therapy may be initiated with 0.5 mg at bedtime, and increased as necessary.

Some patients experience greatest relief when given the entire dose at bedtime; others react more favorably to divided doses, two to four times a day. Frequently, one dose a day is sufficient, and divided doses may be unnecessary or undesirable.

The long duration of action of this drug makes it particularly suitable for bedtime medication when its effects may last throughout the night, enabling patients to turn in bed during the night more easily, and to rise in the morning.

When benztropine mesylate injection, USP is started, do not terminate therapy with other antiparkinsonian agents abruptly. If the other agents are to be reduced or discontinued, it must be done gradually. Many patients obtain greatest relief with combination therapy.

Benztropine mesylate injection, USP may be used concomitantly with, SINEMET (Ccarbidopa-Levodopalevodopa), or with levodopa, in which case dosage adjustment may be required in order to maintain optimum response.

In treating extrapyramidal disorders due to neuroleptic drugs (e.g., phenothiazines), the recommended dosage is 1 to 4 mg once or twice a day parenterally. Dosage must be individualized according to the need of the patient. Some patients require more than recommended; others do not need as much. Drug-Induced Extrapyramidal Disorders:

In acute dystonic reactions, 1 to 2 mL of the injection usually relieves the condition quickly.

When extrapyramidal disorders develop soon after initiation of treatment with neuroleptic drugs (e.g., phenothiazines), they are likely to be transient. One to 2 mg of benztropine mesylate injection, USP two or three times a day usually provides relief within one or two days. If such disorders recur, COGENTIN can be reinstituted.

Certain drug-induced extrapyramidal disorders that develop slowly may not respond to benztropine mesylate injection, USP.

OVERDOSAGE

May be any of those seen in atropine poisoning or antihistamine overdosage: CNS depression, preceded or followed by stimulation; confusion; nervousness; listlessness; intensification of mental symptoms or toxic psychosis in patients with mental illness being treated with neuroleptic drugs (e.g., phenothiazines); hallucinations (especially visual); dizziness; muscle weakness; ataxia; dry mouth; mydriasis; blurred vision; palpitations; tachycardia; elevated blood pressure; nausea; vomiting; dysuria; numbness of fingers; dysphagia; allergic reactions, e.g., skin rash; headache; hot, dry, flushed skin; delirium; coma; shock; convulsions; respiratory arrest; anhidrosis; hyperthermia; glaucoma; constipation. Manifestations:

Physostigmine salicylate, 1 to 2 mg, SC or IV, reportedly will reverse symptoms of anticholinergic intoxication.** A second injection may be given after 2 hours if required. Otherwise treatment is symptomatic and supportive. Maintain respiration. A short-acting barbiturate may be used for CNS excitement, but with caution to avoid subsequent depression; supportive care for depression (avoid convulsant stimulants such as picrotoxin, pentylenetetrazol, or bemegride); artificial respiration for severe respiratory depression; a local miotic for mydriasis and cycloplegia; ice bags or other cold applications and alcohol sponges for hyperpyrexia, a vasopressor and fluids for circulatory collapse. Darken room for photophobia. Treatment:

** Duvoisin, R.C.; Katz, R.J.; Amer. Med. Ass. : 1963-1965, Nov. 25, 1968 206

HOW SUPPLIED

NDC:64725-0012-1 in a CARTON of 5 INJECTIONS

STORAGE AND HANDLING

Store at 20º to 25ºC (68º to 77ºF) [see USP Controlled Room Temperature]. Storage:

Akorn

Distributed by: Akorn, Inc.

Lake Forest, IL 60045

BZ00N Rev. 05/13